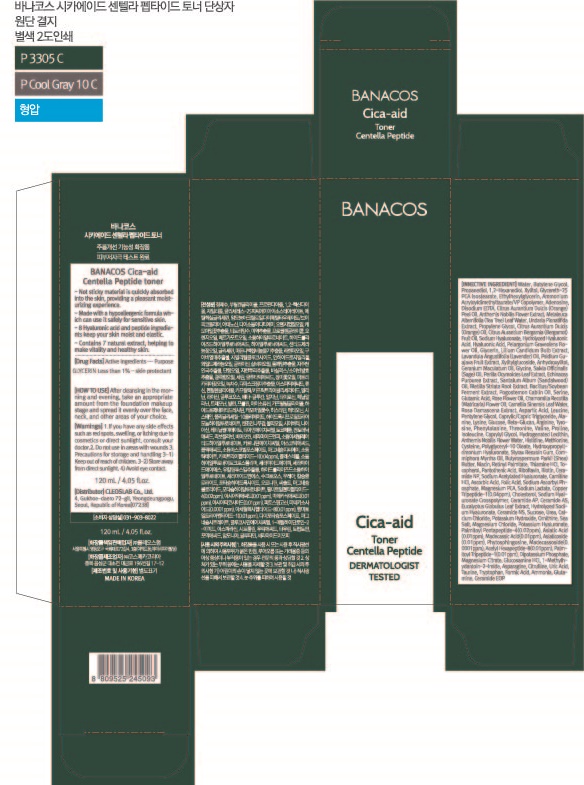 DRUG LABEL: BANACOS Cica-aid Centella Peptide toner
NDC: 79540-311 | Form: LIQUID
Manufacturer: Cleoslab Co.,Ltd
Category: otc | Type: HUMAN OTC DRUG LABEL
Date: 20211219

ACTIVE INGREDIENTS: GLYCERIN 0.002035 g/100 mL
INACTIVE INGREDIENTS: MYRRH OIL 0.0000065 mL/100 mL; SHEA BUTTER 0.000003 mL/100 mL; NIACIN 0.000001 mL/100 mL; ECHINACEA PURPUREA 0.000175 mL/100 mL; THIAMINE HYDROCHLORIDE 0.000001 mL/100 mL; HYDROGENATED SOYBEAN LECITHIN 0.00002 mL/100 mL; POGOSTEMON CABLIN LEAF OIL 0.00015 mL/100 mL; TOCOPHEROL 0.000001 mL/100 mL; BUTYLENE GLYCOL 7.2618405 mL/100 mL; XYLITOL 0.50012 mL/100 mL; AMMONIUM ACRYLOYLDIMETHYLTAURATE/VP COPOLYMER 0.04 mL/100 mL; EDETATE DISODIUM ANHYDROUS 0.0200002 mL/100 mL; VITAMIN A PALMITATE 0.000001 mL/100 mL; RIBOFLAVIN 0.000001 mL/100 mL; BIOTIN 0.000001 mL/100 mL; CERAMIDE NP 0.000001 mL/100 mL; LEVOCARNITINE HYDROCHLORIDE 0.000001 mL/100 mL; GLYCERETH-25 PCA ISOSTEARATE 0.15 mL/100 mL; LAVENDER OIL 0.00105 mL/100 mL; PROPANEDIOL 2.2425 mL/100 mL; 1,2-HEXANEDIOL 2.002147 mL/100 mL; ETHYLHEXYLGLYCERIN 0.05001 mL/100 mL; ADENOSINE 0.04 mL/100 mL; ORANGE OIL 0.01 mL/100 mL; TEA TREE OIL 0.0094 mL/100 mL; UNDARIA PINNATIFIDA 0.005 mL/100 mL; BERGAMOT OIL 0.002725 mL/100 mL; HYALURONIC ACID 0.00250025 mL/100 mL; PELARGONIUM GRAVEOLENS FLOWER OIL 0.00215 mL/100 mL; PROPYLENE GLYCOL 0.0032 g/100 mL; GUAVA 0.001 mL/100 mL; XYLITYLGLUCOSIDE 0.0004 mL/100 mL; FOLIC ACID 0.000001 mL/100 mL; HYALURONATE SODIUM 0.0000001 mL/100 mL; CALCIUM CHLORIDE 0.0000000538 mL/100 mL; POTASSIUM HYDROXIDE 0.00000002 mL/100 mL; MAGNESIUM CHLORIDE 0.0000000234 mL/100 mL; PALMITOYL PENTAPEPTIDE-4 0.00000002 mL/100 mL; ASIATIC ACID 0.00000001 mL/100 mL; MADECASSIC ACID 0.00000001 mL/100 mL; ASIATICOSIDE 0.00000001 mL/100 mL; PHYTOSPHINGOSINE 0.00000001 mL/100 mL; MADECASSOSIDE 0.00000001 mL/100 mL; ACETYL HEXAPEPTIDE-8 0.00000001 mL/100 mL; PALMITOYL TRIPEPTIDE-1 0.00000001 mL/100 mL; TRIAMCINOLONE ACETONIDE 21-DIPOTASSIUM PHOSPHATE 0.00000000916 mL/100 mL; MAGNESIUM CITRATE 0.0000000062 mL/100 mL; GLUCOSAMINE HYDROCHLORIDE 0.000000006 mL/100 mL; MAGNESIUM PIDOLATE 0.0000002628 mL/100 mL; SODIUM LACTATE 0.0000002506 mL/100 mL; CERAMIDE NG 0.0000001 mL/100 mL; SUCROSE 0.0000000838 mL/100 mL; UREA 0.00000007 mL/100 mL; ORNITHINE 0.00000005 mL/100 mL; CHOLESTEROL 0.0000001 mL/100 mL; ANHYDROXYLITOL 0.00028 mL/100 mL; GLYCINE 0.0002450688 mL/100 mL; SAGE OIL 0.0002 mL/100 mL; PERILLA FRUTESCENS LEAF 0.000175 mL/100 mL; SANDALWOOD OIL 0.000175 mL/100 mL; BLETILLA STRIATA TUBER 0.000175 mL/100 mL; SERINE 0.0001360992 mL/100 mL; GLUTAMIC ACID 0.00012600548 mL/100 mL; WATER 87.63048335354 mL/100 mL; TEA LEAF OIL 0.0001 mL/100 mL; ASPARTIC ACID 0.00007901456 mL/100 mL; MEDIUM-CHAIN TRIGLYCERIDES 0.00005 mL/100 mL; LYSINE 0.00004200828 mL/100 mL; CHAMAEMELUM NOBILE FLOWER 0.00979999 mL/100 mL; ARGININE 0.0000380054 mL/100 mL; CHAMOMILE FLOWER OIL 0.0001 mL/100 mL; TYROSINE 0.00003400692 mL/100 mL; LEUCINE 0.00006900744 mL/100 mL; THREONINE 0.00003002052 mL/100 mL; VALINE 0.00003001348 mL/100 mL; PROLINE 0.00003000996 mL/100 mL; ISOLEUCINE 0.0000270064 mL/100 mL; CAPRYLYL GLYCOL 0.000025 mL/100 mL; CHAMAEMELUM NOBILE FLOWER OIL 0.00002 mL/100 mL; HISTIDINE 0.000015018 mL/100 mL; METHIONINE 0.0000115028 g/100 mL; CYSTEINE 0.00001150076 mL/100 mL; POLYGLYCERYL-10 OLEATE 0.00001 mL/100 mL; ALANINE 0.000044042 mL/100 mL; PANTOTHENIC ACID 0.000001 mL/100 mL; LILIUM CANDIDUM BULB 0.002 mL/100 mL; GERANIUM MACULATUM ROOT OIL 0.00025 mL/100 mL; ROSEWOOD OIL 0.000125 mL/100 mL; PENTYLENE GLYCOL 0.00005 mL/100 mL; PHENYLALANINE 0.00003200552 mL/100 mL; STYRAX BENZOIN RESIN 0.0000075 mL/100 mL; SODIUM ACETYLATED HYALURONATE 0.000001 mL/100 mL; ASCORBIC ACID 0.000001 mL/100 mL; SODIUM ASCORBYL PHOSPHATE 0.0000004 mL/100 mL; PREZATIDE COPPER 0.00000022 mL/100 mL; SEA SALT 0.0000000482 mL/100 mL; CREATININE 0.000000005 mL/100 mL; ASPARAGINE 0.00000000472 mL/100 mL; CITRULLINE 0.00000000456 mL/100 mL; URIC ACID 0.000000004 mL/100 mL; TAURINE 0.0000000024 mL/100 mL; TRYPTOPHAN 0.000000002 mL/100 mL; FORMIC ACID 0.0000000012 mL/100 mL; AMMONIA 0.000000001 mL/100 mL; GLUTAMINE 0.0000000008 mL/100 mL; CERAMIDE 1 0.0000000001 mL/100 mL

Toner

BANACOS Cica-aid Centella Peptide toner

Glycerin

stop use and ask a doctor

Take care not to get into the eye.

If you have any side effects such as red spots, swelling or tiching due to cosmetic or direct sunlight, consult your doctor.

PURPOSE

skinprotect

Warning

For external use only

Keep away from fire of flame

Do not spray on clothes because it can stain.

Be caeful not to get into your eyes, and if so wash thoroughly with water

Keep out of reach of children.

indication

sprinkle evenly on your face

do not use in areas with wounds.

avoid eye contact

inactive ingredient

Water, Butylene Glycol,
Propanediol, 1,2-Hexanediol, Xylitol, Glycereth-25
PCA Isostearate, Ethylhexylglycerin, Ammonium
Acryloyldimethyltaurate/VP Copolymer, Adenosine,
Disodium EDTA, Citrus Aurantium Dulcis (Orange)
Peel Oil, Anthemis Nobilis Flower Extract, Melaleuca
Alternifolia (Tea Tree) Leaf Water, Undaria Pinnatifida
Extract, Propylene Glycol, Citrus Aurantium Dulcis
(Orange) Oil, Citrus Aurantium Bergamia (Bergamot)
Fruit Oil, Sodium Hyaluronate, Hydrolyzed Hyaluronic
Acid, Hyaluronic Acid, Pelargonium Graveolens Flo-
wer Oil, Glycerin, Lilium Candidum Bulb Extract,
Lavandula Angustifolia (Lavender) Oil, Psidium Gu-
ajava Fruit Extract, Xylitylglucoside, Anhydroxylitol,
Geranium Maculatum Oil, Glycine, Salvia Officinalis
(Sage) Oil, Perilla Ocymoides Leaf Extract, Echinacea
Purpurea Extract, Santalum Album (Sandalwood)
Oil, Bletilla Striata Root Extract, Bacillus/Soybean
Ferment Extract, Pogostemon Cablin Oil, Serine,
Glutamic Acid, Rose Flower Oil, Chamomilla Recutita
(Matricaria) Flower Oil, Camellia Sinensis Leaf Water,
Rosa Damascena Extract, Aspartic Acid, Leucine,
Pentylene Glycol, Caprylic/Capric Triglyceride, Ala-
nine, Lysine, Glucose, Beta-Glucan, Arginine, Tyro-
sine, Phenylalanine, Threonine, Valine, Proline,
Isoleucine, Caprylyl Glycol, Hydrogenated Lecithin,
Anthemis Nobilis Flower Water, Histidine, Methionine,
Cysteine, Polyglyceryl-10 Oleate, Hydroxypropylt-
rimonium Hyaluronate, Styrax Benzoin Gum, Com-
miphora Myrrha Oil, Butyrospermum Parkii (Shea)
Butter, Niacin, Retinyl Palmitate, Thiamine HCl, To-
copherol, Pantothenic Acid, Riboflavin, Biotin, Cera-
mide NP, Sodium Acetylated Hyaluronate, Carnitine
HCl, Ascorbic Acid, Folic Acid, Sodium Ascorbyl Ph-
osphate, Magnesium PCA, Sodium Lactate, Copper
Tripeptide-1(0.04ppm), Cholesterol, Sodium Hyal-
uronate Crosspolymer, Ceramide AP, Ceramide AS,
Eucalyptus Globulus Leaf Extract, Hydrolyzed Sodi-
um Hyaluronate, Ceramide NS, Sucrose, Urea, Cal-
cium Chloride, Potassium Hydroxide, Ornithine, Sea
Salt, Magnesium Chloride, Potassium Hyaluronate,
Palmitoyl Pentapeptide-4(0.02ppm), Asiatic Acid
(0.01ppm), Madecassic Acid(0.01ppm), Asiaticoside
(0.01ppm), Phytosphingosine, Madecassoside(0.
0001ppm), Acetyl Hexapeptide-8(0.01ppm), Palm-
itoyl Tripeptide-1(0.01ppm), Dipotassium Phosphate,
Magnesium Citrate, Glucosamine HCl, 1-Methylh-
ydantoin-2-Imide, Asparagine, Citrulline, Uric Acid,
Taurine, Tryptophan, Formic Acid, Ammonia, Gluta-
mine, Ceramide EOP

Direction

After cleansing in the morning and evening take an appropriate amount from the foundation makeup stage and spread it evenly over the face, neck, and other areas of your choice.

label

79540-311-01